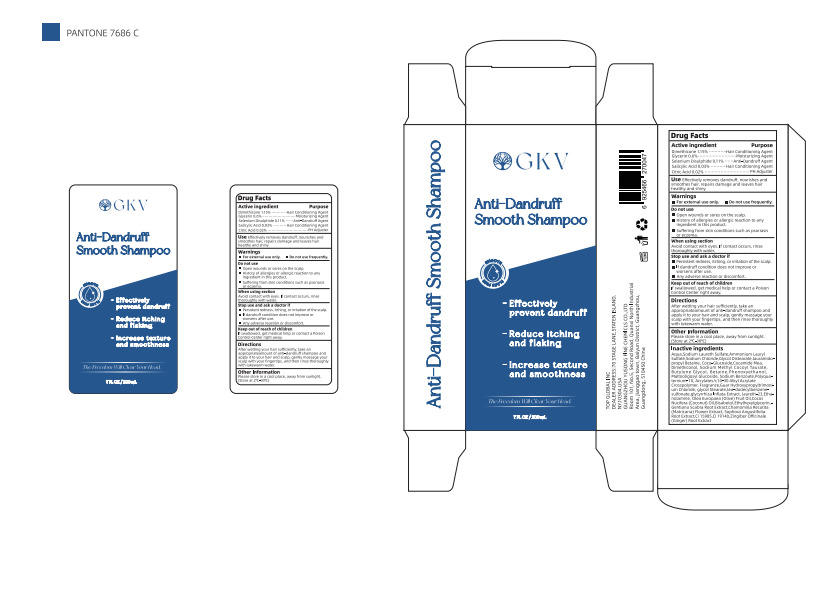 DRUG LABEL: GKV Anti Dandruff Smooth
NDC: 84558-001 | Form: SHAMPOO
Manufacturer: GUANGZHOU YUSONG FINE CHEMICLS Co., Ltd
Category: otc | Type: HUMAN OTC DRUG LABEL
Date: 20240801

ACTIVE INGREDIENTS: SODIUM BENZOATE 0.4 g/100 mL; SODIUM CHLORIDE 1.15 g/100 mL; GLYCERIN 0.6 g/100 mL; SELENIUM SULFIDE 0.11 g/100 mL; SALICYLIC ACID 0.03 g/100 mL; CITRIC ACID MONOHYDRATE 0.02 g/100 mL; DIMETHICONE 1.15 g/100 mL
INACTIVE INGREDIENTS: BETAINE; SOPHORA FLAVESCENS ROOT; WATER; GUAR HYDROXYPROPYLTRIMONIUM CHLORIDE; OLIVE OIL; AMMONIUM LAURYL SULFATE; GLYCOL DISTEARATE; MALTOOLIGOSYL GLUCOSIDE; TRIETHANOLAMINE DODECYLBENZENESULFONATE; GINKGO; DIMETHICONOL (2000 CST); FD&C YELLOW NO. 6; COCONUT OIL; CHAMOMILE; SODIUM METHYL COCOYL TAURATE; GENTIANA SCABRA ROOT; ACRYLATES/C10-30 ALKYL ACRYLATE CROSSPOLYMER (60000 MPA.S); GLYCOL STEARATE; 2-AMINOETHANOL; ETHYLHEXYLGLYCERIN; FD&C YELLOW NO. 5; BUTYLENE GLYCOL; GINGER; SODIUM LAURETH SULFATE; LAURAMIDOPROPYL BETAINE; LEVOMENOL; PHENOXYETHANOL; POLYQUATERNIUM-10 (10000 MPA.S AT 2%); LAURETH-23; COCO GLUCOSIDE; COCO MONOETHANOLAMIDE

84558-001

Active Ingredient(s)

Dimethicone 1.15%
Glycerin 0.6%
Selenium Disulphide 0.11% .
Salicylic Acid 0.03%
Citric Acid 0.02%

Purpose

Hair Conditioning Agent
Moisturizing Agent
Anti-Dandruff Agent
Hair Conditioning Agent
PH Adjuster

Use

Use Effectively removes dandruff, nourishes and smoothes hair, repairs damage and leaves hair healthy and shiny

Warnings

1. For external use only

2. Do not use frequently.

Do not use

1.Open wounds or sores on the scalp.
2.History of allergies or allergic reaction to any ingredient in this product.
3.suffering from skin conditions such as psoriasis or eczema. .

WHEN USING

Avoid contact with eyes. If contact occurs, rinse thoroughly with water.

STOP USE

1. Persistent redness, itching, or iritation of the scalp.
2. If dandruff condition does not improve or worsens after use.
3. Any adverse reaction or discomfort.

KEEP OUT OF REACH OF CHILDREN

If swallowed, get medical help or contact a Poison Control Center right away.

Directions

After wetting your hair sufficiently, take an appropriateamount of anti-dandruff shampoo and apply it to your

hair and scalp, gently massage your scalp with your fingertips, and then rinse thoroughly with lukewarm water.

Other information

Please store in aco (store at 2°C-30°C）

Inactive ingredients

Aqua, Sodium Laureth Sulfate,Ammonium Lauryl Sulfate,Sodium Chloride,Glycol Distearate, lauramido-
propyl Betaine, Coco-Glucoside,Cocamide Mea, Dimethiconol, Sodium Taurine Cocoyl Methyltau-
rate,Butylene Glycol, Betaine,Phenoxyethanol, Maltooligosyl Glucoside, Sodium Benzoate,Polyqua-
ternium-10, Acrylates/c10-30 Alkyl Acrylate Crosspolymer, Fragrance,Guar Hydroxypropyltrimoni-
um Chloride, glycol Stearate,tea -dodecylbenzene- sulfonate,glycyrrhiza Inflata Extract, laureth-23,Etha-
nolamine, Olea Europaea (Olive) Fruit Oil,Cocos Nucifera (Coconut) oil,Bisabolol,Ethylhexylglycerin,- |
Gentiana Scabra Root Extract,Chamomilla Recutita (Matricaria) Flower Extract, Sophora Angustifolia
Root Extract,Ci 15985,Ci 19140,Zingiber Officinale (Ginger) Root Extract